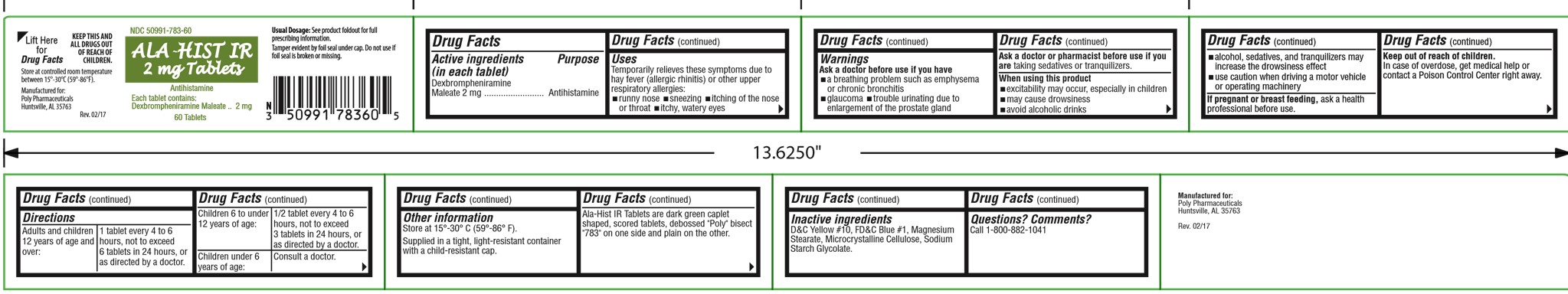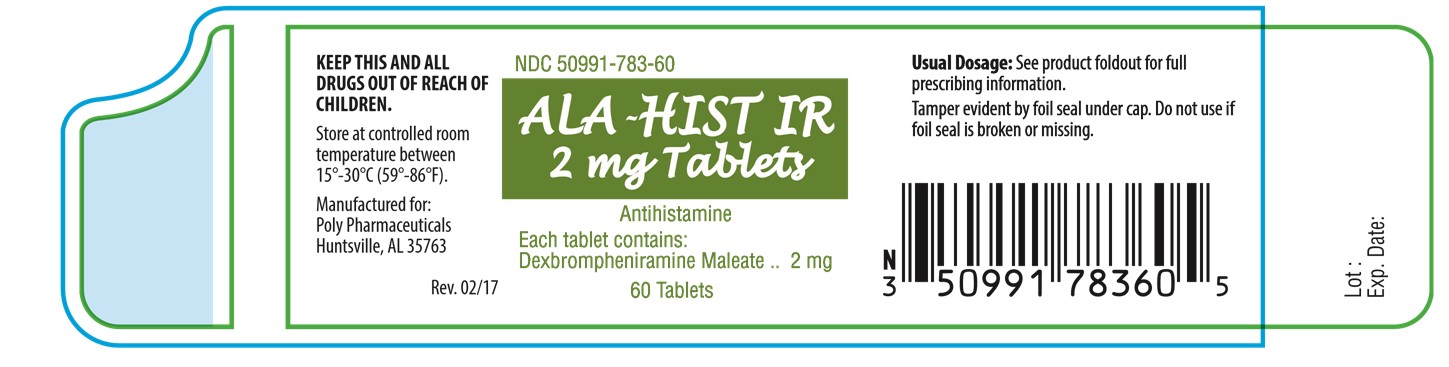 DRUG LABEL: ALA-HIST IR
NDC: 50991-783 | Form: TABLET
Manufacturer: Poly Pharmaceuticals, Inc.
Category: otc | Type: HUMAN OTC DRUG LABEL
Date: 20251203

ACTIVE INGREDIENTS: DEXBROMPHENIRAMINE MALEATE 2 mg/1 1
INACTIVE INGREDIENTS: CALCIUM PHOSPHATE, DIBASIC, DIHYDRATE; SILICON DIOXIDE; CELLULOSE, MICROCRYSTALLINE; CROSCARMELLOSE SODIUM; MAGNESIUM STEARATE

ALA-HIST IR 2 mg Tablets

Drug Facts

Active ingredients

(in each tablet)

Dexbrompheniramine Maleate 2 mg

Purpose

Antihistamine

Uses

Temporarily relieves these symptoms due to hay fever (allergic rhinitis) or upper respiratory allergies:

- runny nose
- sneezing
- itching of the nose or throat
- itchy, watery eyes

Warnings

Ask a doctor before use if you have

- a breathing problem such as emphysema or chronic bronchitis
- glaucoma
- trouble urinating due to enlargement of the prostate gland

Ask a doctor or pharmacist before use if you are taking sedatives or tranquilizers.

When using this product

- excitability may occur, especially in children
- may cause drowsiness
- avoid alcoholic drinks
- alcohol, sedatives, and tranquilizers may increase the drowsiness effect
- use caution when driving a motor vehicle or operating machinery

PREGNANCY OR BREAST FEEDING

If pregnant or breast-feeding, ask a health professional before use.

Keep out of reach of children.

In case of overdose, get medical help or contact a Poison Control Center right away.

Directions

Adults and children 12 years of age and over: | 1 tablet every 4 to 6 hours, not to exceed 6 tablets in 24 hours.
Children 6 to under 12 years of age: | 1/2 tablet every 4 to 6 hours, not to exceed 3 tablets in 24 hours.
Children under 6 years of age: | Consult a doctor.

Other information

Store at 15° - 30°C (59° - 86°F).

Supplied in a tight, light-resistant container with a child-resistant cap.

Contains color additives including FD&C Yellow No. 5 (tartrazine).

Ala-Hist IR Tablets are dark green caplet shaped, scored tablets, debossed "Poly" bisect "783" on one side and plain on the other.

Inactive ingredients

colloidal silicon dioxide, croscarmellose sodium, dibasic calcium phosphate dihydrate, FD&C Blue #1 aluminum lake, FD&C Yellow #5 aluminum lake, magnesium stearate, and silicified microcrystalline cellulose.

Questions?

Call 1-800-882-1041

Manufactured for:
Poly Pharmaceuticals
Quitman, MS 39355

Rev. 02/12

Product Packaging

The packaging below represents the labeling currently used.

Principal display panel and side panel for 60 tablets label:

NDC 50991-783-60

ALA-HIST IR
2 mg Tablets

Antihistamine

Each tablet contains:
Dexbrompheniramine Maleate.........2 mg

60 Tablets

Usual Dosage: See product foldout for full
prescribing information

Tamper evident by foil seal under cap. Do not

use if foil seal is broken or missing.

KEEP THIS AND ALL DRUGS OUT OF
REACH OF CHILDREN.
Store at controlled room temperature 15°-30°C
(59°-86°F).

Manufactured for:
Poly Pharmaceuticals

Rev. 02/12